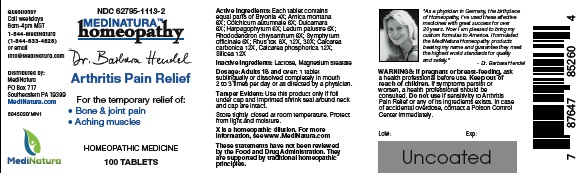 DRUG LABEL: Dr. Hendel Arthritis Pain Relief
NDC: 62795-1113 | Form: TABLET
Manufacturer: MediNatura Inc
Category: homeopathic | Type: HUMAN OTC DRUG LABEL
Date: 20221004

ACTIVE INGREDIENTS: BRYONIA ALBA ROOT 4 [hp_X]/1 1; ARNICA MONTANA 6 [hp_X]/1 1; COLCHICUM AUTUMNALE BULB 6 [hp_X]/1 1; SOLANUM DULCAMARA TOP 6 [hp_X]/1 1; HARPAGOPHYTUM PROCUMBENS ROOT 6 [hp_X]/1 1; LEDUM PALUSTRE TWIG 6 [hp_X]/1 1; RHODODENDRON AUREUM LEAF 6 [hp_X]/1 1; COMFREY ROOT 6 [hp_X]/1 1; TOXICODENDRON PUBESCENS LEAF 8 [hp_X]/1 1; OYSTER SHELL CALCIUM CARBONATE, CRUDE 12 [hp_X]/1 1; TRIBASIC CALCIUM PHOSPHATE 12 [hp_X]/1 1; SILICON DIOXIDE 3 [hp_X]/1 1
INACTIVE INGREDIENTS: LACTOSE MONOHYDRATE; MAGNESIUM STEARATE

Dr. Hendel Arthritis Pain Relief

WARNINGS

If pregnant or breast-feeding, ask a health professional before use. Keep out of reach of children. If symptoms persist or

worsen, a health professional should be consulted. Do not use if sensitivity to Hendel Arthritis Pain Relief or any of its ingredients exists. In case of accidental overdose, contact a Poison Control Center immediately.

KEEP OUT OF REACH OF CHILDREN

INDICATIONS

Arthritis Pain Relief

ACTIVE INGREDIENT

Each tablet containsequal parts of: Bryonia 4X; Arnica montana 6X; Colchicum autumnale 6X; Dulcamara 6X; Harpagophytum 6X; Ledum palustre 6X; Rhododendron chrysanthum 6X; Symphytum officinale 6X; Rhus tox 8X, 12X, 30X; Calcarea carbonica 12X, Calcarea phosphorica 12X; Silicea 12X

INACTIVE INGREDIENT

Lactose, Magnesium stearate

DIRECTIONS

Dosage: Adults 18 and over: 1 tablet sublingually or dissolved completely in mouth 2 to 3 times per day or as directed by a physician.

USES

For the temporary relief of:

• Bone & joint pain

• Aching muscles

PACKAGE LABEL

Add image transcription here...